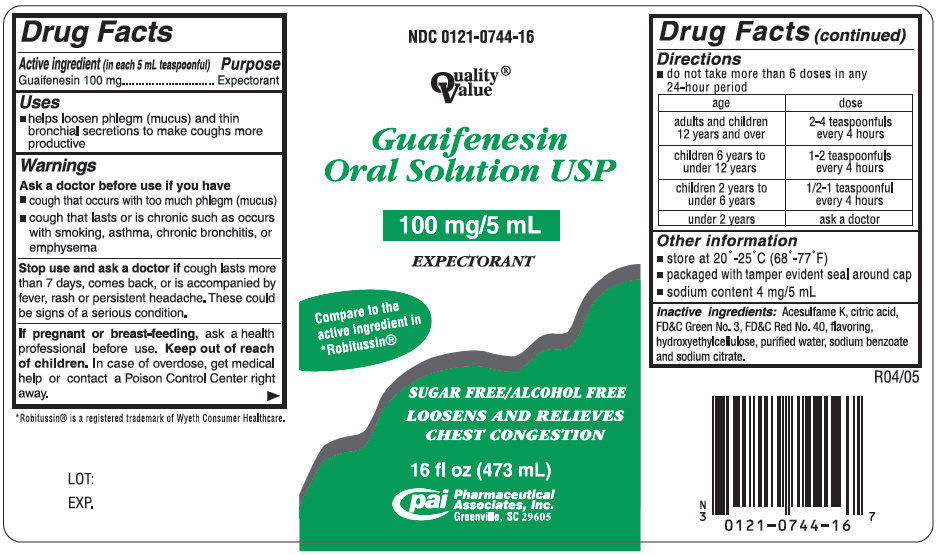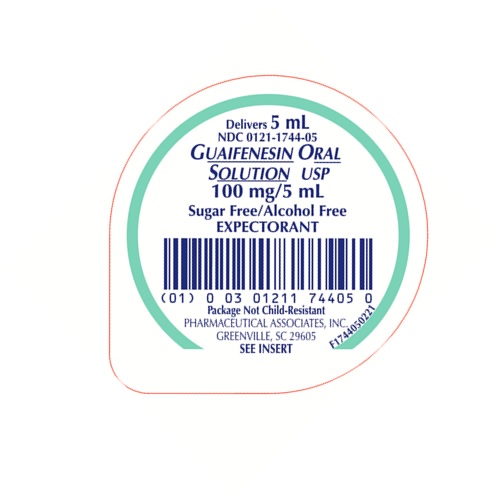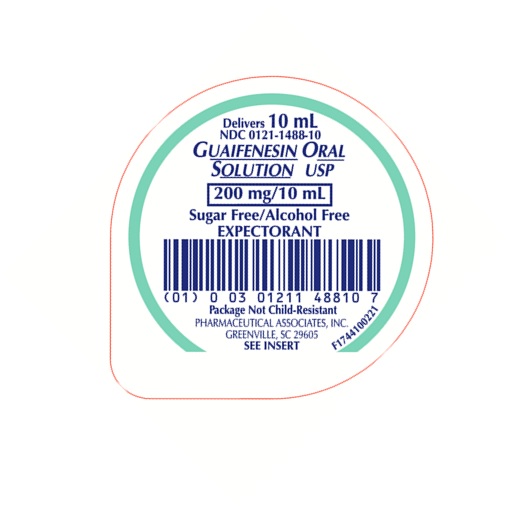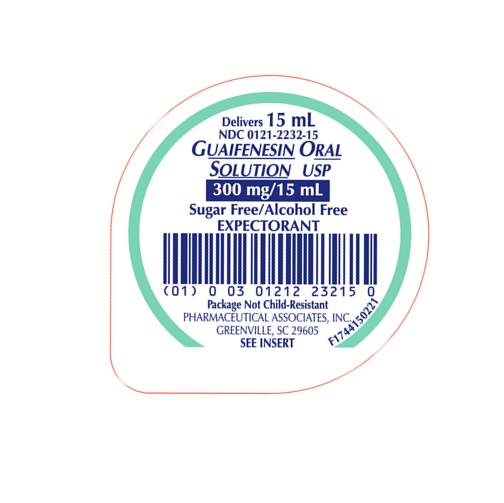 DRUG LABEL: GUAIFENESIN
NDC: 0121-0744 | Form: SOLUTION
Manufacturer: PAI Holdings, LLC dba PAI Pharma
Category: otc | Type: HUMAN OTC DRUG LABEL
Date: 20220614

ACTIVE INGREDIENTS: GUAIFENESIN 100 mg/5 mL
INACTIVE INGREDIENTS: ACESULFAME POTASSIUM; FD&C GREEN NO. 3; FD&C RED NO. 40; HYDROXYETHYL CELLULOSE, UNSPECIFIED; WATER; SODIUM BENZOATE; SODIUM CITRATE, UNSPECIFIED FORM; ANHYDROUS CITRIC ACID

GUAIFENESIN

PURPOSE

Expectorant
SUGAR FREE / ALCOHOL FREE

DESCRIPTION

Each 5 mL (1 teaspoonful) contains:
Guaifenesin 100 mg

Inactive Ingredients

Acesulfame K, citric acid, FD&C Green No. 3, FD&C Red No. 40, flavoring, hydroxyethylcellulose, purified water, sodium benzoate and sodium citrate.

Sodium Content: 4 mg/5 mL

USES

Helps loosen phlegm (mucus) and thin bronchial secretions to make coughs more productive.

WARNINGS

Ask a doctor before use if you have

- cough that occurs with too much phlegm (mucus)
- cough that lasts or is chronic such as occurs with smoking, asthma, chronic bronchitis, or emphysema

Stop use and ask a doctor if

- cough lasts more than 7 days, comes back, or is accompanied by fever, rash, or persistent headache. These could be signs of a serious condition.
- you are hypersensitive to any of the ingredients.

PREGNANCY OR BREAST FEEDING

If pregnant or breast-feeding, ask a health professional before use.

Keep out of reach of children. In case of overdose, get medical help or contact a Poison Control Center right away.

Professional Note

Guaifenesin has been shown to produce a color interference with certain clinical laboratory determinations of 5-hydroxyindoleacetic acid (5-HIAA) and vanillylmandelic acid (VMA).

DIRECTIONS

Follow dosage below or use as directed by a physician.

- do not take more than 6 doses in any 24-hour period.

age | dose
adults and children 12 years and over | 10 to 20 mL (2 to 4 teaspoonfuls) every 4 hours
children 6 years to under 12 years | 5 to 10 mL (1 to 2 teaspoonfuls) every 4 hours
children 2 to under 6 years of age | 2.5 to 5 mL (½ to 1 teaspoonful) every 4 hours
children under 2 years of age | consult a physician

HOW SUPPLIED

Guaifenesin Oral Solution USP is a red, raspberry flavored solution supplied in the following oral dosage forms:

NDC 0121-0744-04: 4 fl oz (120 mL) bottle
NDC 0121-0744-08: 8 fl oz (237 mL) bottle
NDC 0121-0744-16: 16 fl oz (473 mL) bottle

NDC 0121-1744-05: 5 mL unit dose cup
NDC 0121-1744-00: Case contains 100 unit dose cups of 5 mL (0121-1744-05) packaged in 10 trays of 10 unit dose cups each.

NDC 0121-1488-10: 10 mL unit dose cup
NDC 0121-1488-00: Case contains 100 unit dose cups of 10 mL (0121-1488-10) packaged in 10 trays of 10 unit dose cups each.

NDC 0121-2232-15: 15 mL unit dose cup
NDC 0121-2232-00: Case contains 100 unit dose cups of 15 mL (0121-2232-15) packaged in 10 trays of 10 unit dose cups each.

STORAGE

Keep tightly closed. Store at controlled room temperature, 20°-25°C (68°-77°F). [See USP] Protect from light.

PRINCIPAL DISPLAY PANEL - 473 mL Bottle Label

NDC 0121-0744-16

Quality®
Value

Guaifenesin Oral Solution USP

100 mg/5 mL

EXPECTORANT

Compare to the
active ingredient in
*Robitussin®

SUGAR FREE/ALCOHOL FREE
LOOSENS AND RELIEVES
CHEST CONGESTION

16 fl oz (473 mL)

Pharmaceutical
Associates, Inc.
Greenville, SC 29605

PRINCIPAL DISPLAY PANEL - 5 mL Cup Label

Delivers 5 mL

NDC 0121-1744-05

G UAIFENESIN O RAL S OLUTION USP

100 mg/5 mL

Sugar Free/Alcohol Free

EXPECTORANT

Package Not Child-Resistant

PHARMACEUTICAL ASSOCIATES, INC.
GREENVILLE, SC 29605

SEE INSERT

PRINCIPAL DISPLAY PANEL - 10 mL Cup Label

Delivers 10 mL

NDC 0121-1488-10

G UAIFENESIN O RAL S OLUTION USP

200 mg/10 mL

Sugar Free/Alcohol Free

EXPECTORANT

Package Not Child-Resistant

PHARMACEUTICAL ASSOCIATES, INC.
GREENVILLE, SC 29605

SEE INSERT

PRINCIPAL DISPLAY PANEL - 15 mL Cup Label

Delivers 15 mL

NDC 0121-2232-15

G UAIFENESIN O RAL S OLUTION USP

300 mg/15 mL

Sugar Free/Alcohol Free

EXPECTORANT

Package Not Child-Resistant

PHARMACEUTICAL ASSOCIATES, INC.
GREENVILLE, SC 29605

SEE INSERT